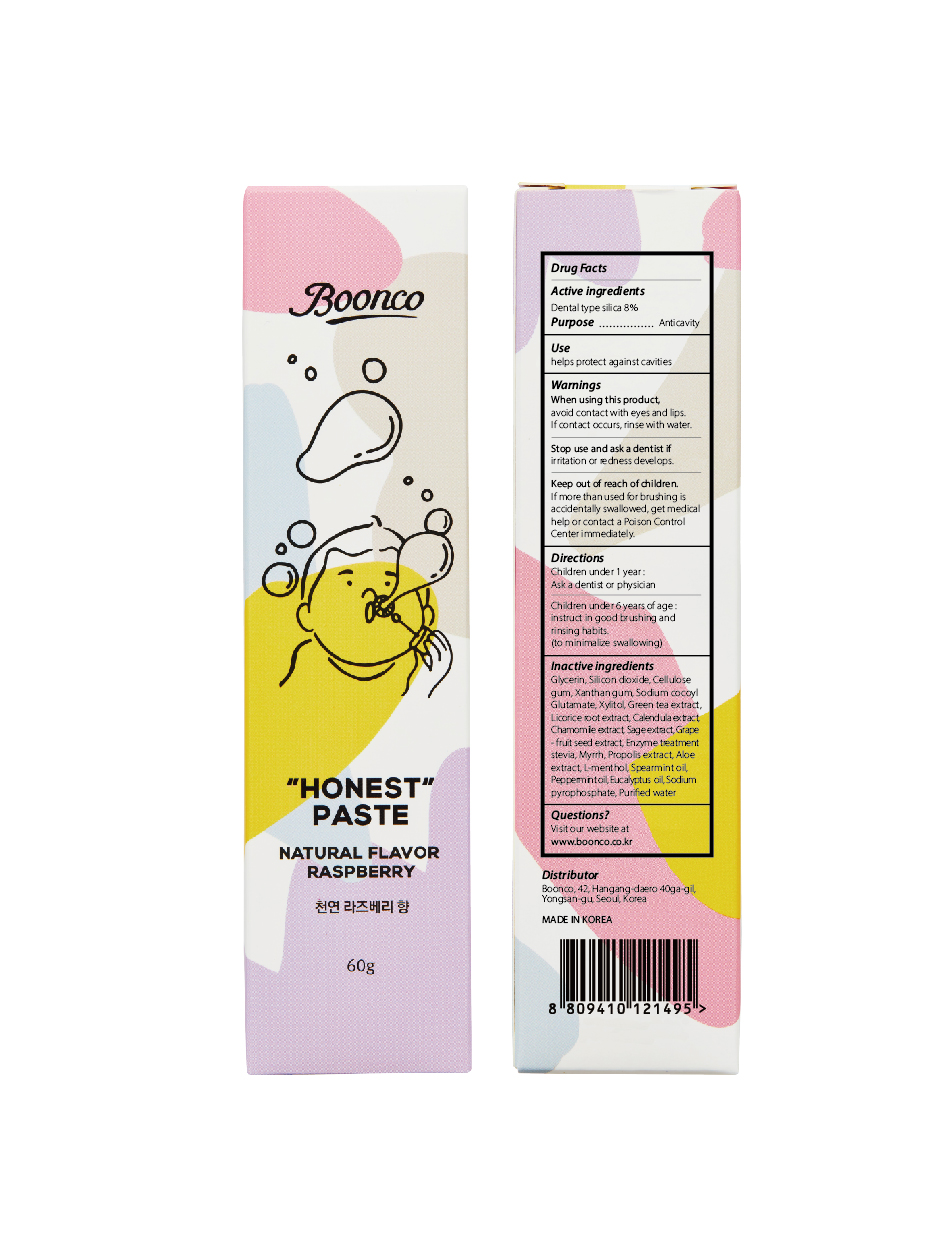 DRUG LABEL: Honest-Paste Kids
NDC: 80925-201 | Form: PASTE
Manufacturer: BOONCO Co., Ltd
Category: otc | Type: HUMAN OTC DRUG LABEL
Date: 20220107

ACTIVE INGREDIENTS: SILICON DIOXIDE 8 g/100 g
INACTIVE INGREDIENTS: GLYCERIN; ASCORBIC ACID; LEVOMENTHOL; CARBOXYMETHYLCELLULOSE SODIUM; GREEN TEA LEAF; ROSEMARY; SORBITOL; WATER; SCUTELLARIA BAICALENSIS ROOT; XYLITOL; CALENDULA OFFICINALIS FLOWER; CHAMOMILE

80925-201

Active ingredients

Dental type silica 8%

Purpose

Anticavity

Use

helps protect against cavities

Warnings

When using this product, avoid contact with eyes and lips. If contact occurs, rinse with water.

Stop use and ask a dentist if

irritation or redness develops.

Keep out of reach of children.

If more than used for brushing is accidentally swallowed, get medical help or contact a Poison Control Center immediately.

Directions

- children under 1 year: ask a dentist or physician
- children under 6 years: instruct in good brushing and rinsing habits (to minimize swallowing)

Inactive ingredients

glycerin, cellulose gum, ascorbic acid, rosemary extract, scutellaria root extract, green tea extract, xylitol, calendula extract, chamomile extract, enzyme treatment stevia, l-menthol, raspberry flavor, sorbitol, purified water